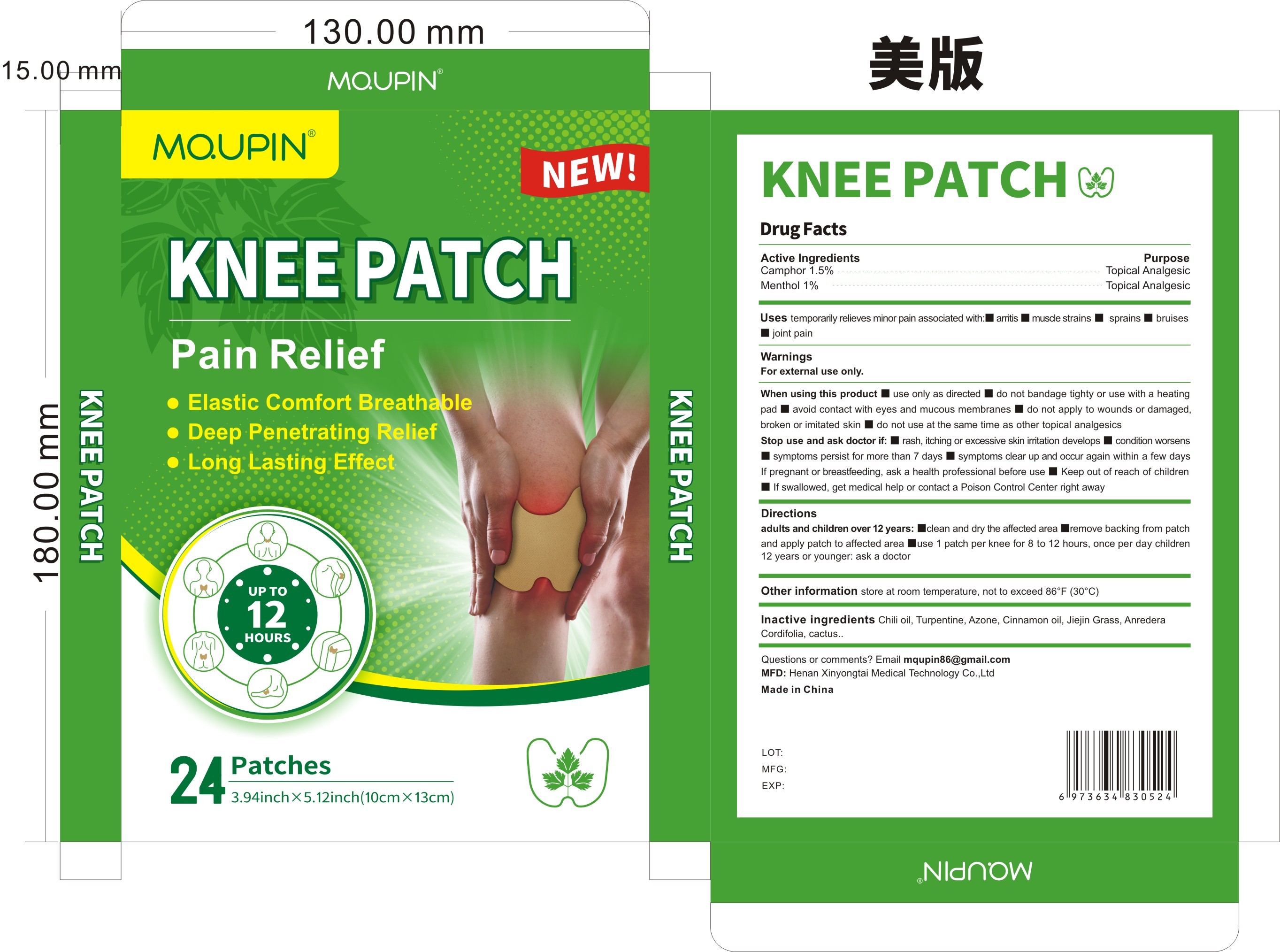 DRUG LABEL: Mqupin Knee Patch Pain Relife
NDC: 83778-004 | Form: PATCH
Manufacturer: Nanchang Dental Bright Technology Co.,Ltd.
Category: otc | Type: HUMAN OTC DRUG LABEL
Date: 20250324

ACTIVE INGREDIENTS: BORNEOL 1.5 g/100 1; MENTHOL 1 g/100 1
INACTIVE INGREDIENTS: CINNAMON OIL; GRASS CARP; ANREDERA CORDIFOLIA LEAF; TURPENTINE; CAPSICUM; LAUROCAPRAM; HOODIA GORDONII SAP

83778-004 Update V2

Active Ingredient

Camphor 1.5%
Menthol 1%

Purpose

Topical Analgesic

Use

temporarily relieves minor pain associated with:

■arthritis

■muscle strains

■sprains

■bruises

■ joint pain

Warnings

For external use only.

do not use at the same time as other topical analgesics

When Using

■ use only as directed

■ do not bandage tighty or use with a heating pad

■ avoid contact with eyes and mucous membranes

■ do not apply to wounds or damaged, broken or imitated skin

■ do not use at the same time as other topical analgesics

Stop Use

■ rash, itching or excessive skin irritation develops

■ condition worsens

■ symptoms persist for more than 7 days

■ symptoms clear up and occur again within a few days If pregnant or breastfeeding, ask a health professional before use

■ Keep out of reach of children

■ If swallowed, get medical help or contact a Poison Control Center right away

Ask Doctor

■ Keep out of reach of children

■ If swallowed, get medical help or contact a Poison Control Center right away

Keep Out Of Reach Of Children

Directions

adults and children over 12 years:

■clean and dry the affected area

■remove backing from patch and apply patch to affected area

■use 1 patch per knee for 8 to 12 hours, once per day

Other information

store at room temperature, not to exceed 86°F (30°C)

Inactive ingredients

Chili oil, Turpentine, Azone, Cinnamon oil, Jiejin Grass, Anredera Cordifolia，cactus.

Questions

mqupin86@gmail.com